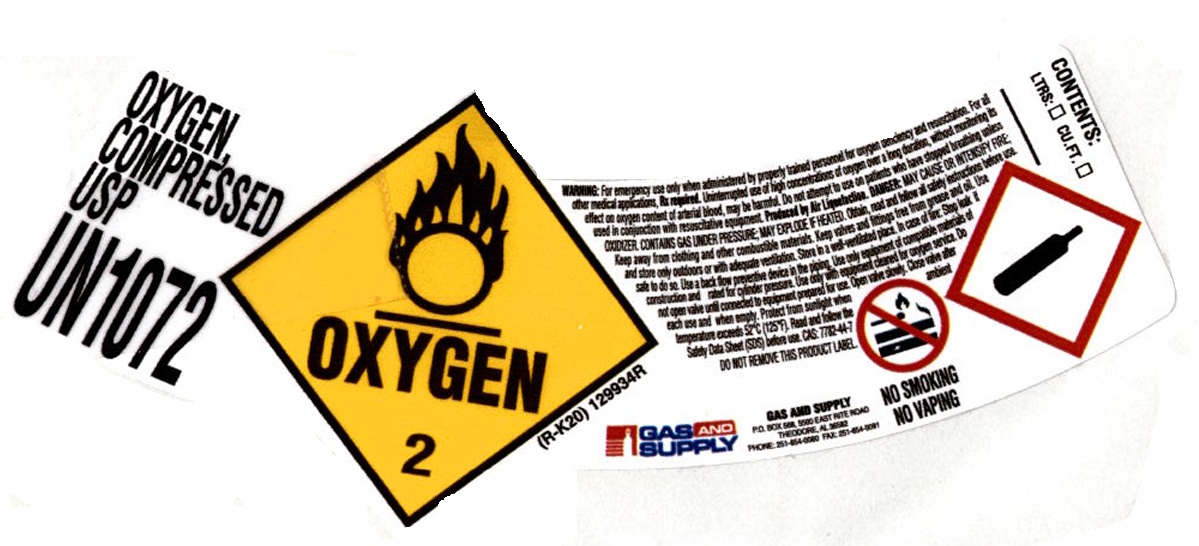 DRUG LABEL: Oxygen
NDC: 71654-005 | Form: GAS
Manufacturer: SOUTHERN GAS AND SUPPLY, INC. dba Gas and Supply
Category: prescription | Type: HUMAN PRESCRIPTION DRUG LABEL
Date: 20251208

ACTIVE INGREDIENTS: OXYGEN 995 mL/1 L

Oxygen

PACKAGE LABEL

OXYGEN, COMPRESSED USP

UN1072

WARNING: For emergency use only when administered by properly trained personnel for oxygen deficiency and resuscitation. For all other medical applications, Rx required. Uninterrupted use of high concentrations of oxygen over a long duration, without monitoring its effect on oxygen content of arterial blood, may be harmful. Do not attempt to use on patients who have stopped breathing unless used in conjunction with resuscitative equipment. Produced by Air Liquefaction. DANGER: MAY CAUSE OR INTENSIFY FIRE; OXIDIZER. CONTAINS GAS UNDER PRESSURE; MAY EXPLODE IF HEATED. Do not handle until all safety precautions have been read and understood. Keep and store away from clothing and other combustible materials. Keep valves and fittings free from grease and oil. Use and store only outdoors or in a well-ventilated place. In case of fire: stop leak if safe to do so. Use a back flow preventive device in the piping. Use only with equipment of compatible materials of construction and rated for cylinder pressure. Use only with equipment cleaned for oxygen service. Open valve slowly. Close valve after each use and when empty. Protect from sunlight when ambient temperature exceeds 52 degrees C (125 degrees F). Read and follow the Safety Data Sheet (SDS) before use. CAS: 7782-44-7 DO NOT REMOVE THIS PRODUCT LABEL.
GAS AND SUPPLY
GAS AND SUPPLY
P.O. BOX 568, 5500 EAST RITE ROAD
THEODORE, AL 36582
PHONE: 251-654-0080 FAX 251-654-0091

NO SMOKING

NO VAPING

CONTENTS: LTRS: CU.FT.